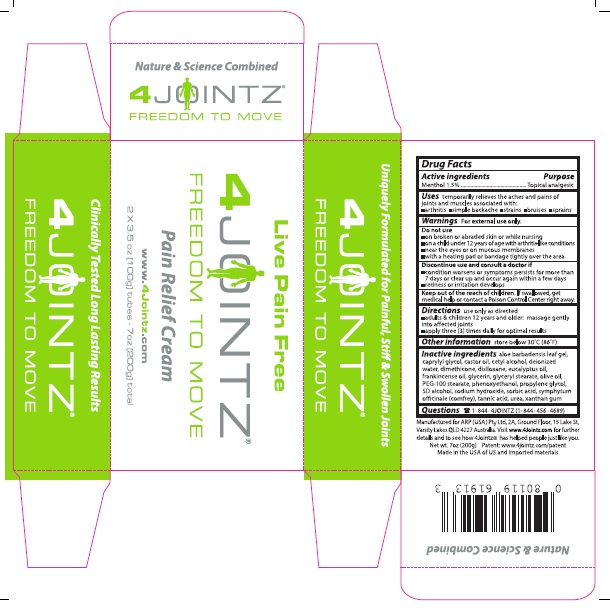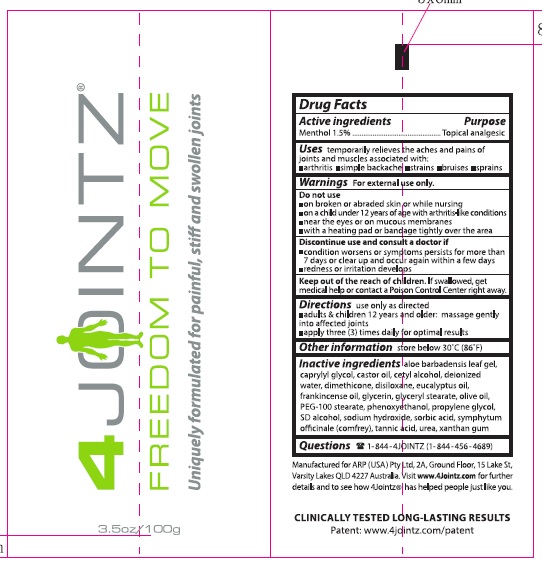 DRUG LABEL: 4Jointz
NDC: 71282-011 | Form: CREAM
Manufacturer: ARP(USA) Pty Ltd
Category: otc | Type: HUMAN OTC DRUG LABEL
Date: 20241228

ACTIVE INGREDIENTS: MENTHOL 1.5 g/100 g
INACTIVE INGREDIENTS: ALOE VERA LEAF; CAPRYLYL GLYCOL; CASTOR OIL; CETYL ALCOHOL; DIMETHICONE; HEXAMETHYLDISILOXANE; EUCALYPTUS OIL; FRANKINCENSE OIL; GLYCERIN; GLYCERYL MONOSTEARATE; OLIVE OIL; PEG-100 STEARATE; PHENOXYETHANOL; PROPYLENE GLYCOL; ALCOHOL; SODIUM HYDROXIDE; SORBIC ACID; SYMPHYTUM OFFICINALE WHOLE; TANNIC ACID; UREA; WATER; XANTHAN GUM

4Jointz®

Drug Facts

Active ingredients

Menthol 1.5%

Purpose

Topical analgesic

INDICATIONS AND USAGE

Uses Temporarily relieves the aches and pains of muscles and joints associated with:

■ arthritis ■ simple backache ■ strains ■ bruises ■ sprains

Warnings For external use only.

Do not use

■ on open wounds or abraded skin or while nursing

■ on a child under 12 years of age with arthritis-like conditions

■ near the eyes or on mucous membranes

■ with a heating pad or bandage tightly over the area

Discontinue use and consult a doctor if

■ conditions worsen or symptoms persists for more than

7 days or clear up and occur again within a few days

■ redness or irritation develops

KEEP OUT OF REACH OF CHILDREN

Keep out of the reach of children. If swallowed,

get medical help or contact a Poison Control Center right away.

DOSAGE AND ADMINISTRATION

Directions Use only as directed

■ adults & children 12 years and older: massage gently

into affected joints

■ apply three (3) times daily for optimal results

Other Information store below 30°C (86°F)

Inactive Ingredients

Inactive ingredients Aloe barbadensis leaf gel,

caprylyl glycol, castor oil, cetyl alcohol, deionized

water, dimethicone, disiloxane,eucalypyus oil,

frankincense oil, glycerin, glyceryl stearate, olive oil,

PEG-100 stearate, phenoxyethanol, propylene glycol,

SD alcohol, sodium hydroxide, sorbic acid, symphytum

officinale (comfrey), tannic acid, urea, xanthan gum

Questions

1-844-4JOINTZ (1-844-456-4689)

4JOINTZ®

Principal Display Panel

Live Pain Free

4JOINTZ®
FREEDOM TO MOVE

Pain Relief Cream

www.4jointz.com

2 X 3.5 oz [100g] tubes – 7 oz [200g] total

Clinically Tested Long Lasting Results

4JOINTZ®
FREEDOM TO MOVE

Uniquely Formulated for Painful, Stiff & Swollen Joints

4JOINTZ®
FREEDOM TO MOVE

Nature & Science Combined
4JOINTZ®
FREEDOM TO MOVE

Nature & Science Combined

0 80119 61913 3

Manufactured for ARP (USA) Pty Ltd, 2A, Ground Floor, 15 Lake St.

Varsity Lakes QLD 4227 Australia. Visit www.4Jointz.com for further

details and to see how 4Jointz has helped people just like you.

Net wt. 7oz (200g). Patent: www.4jointz.com/patent

Made in the USA of US and imported materials

↓Inner Package↓

res